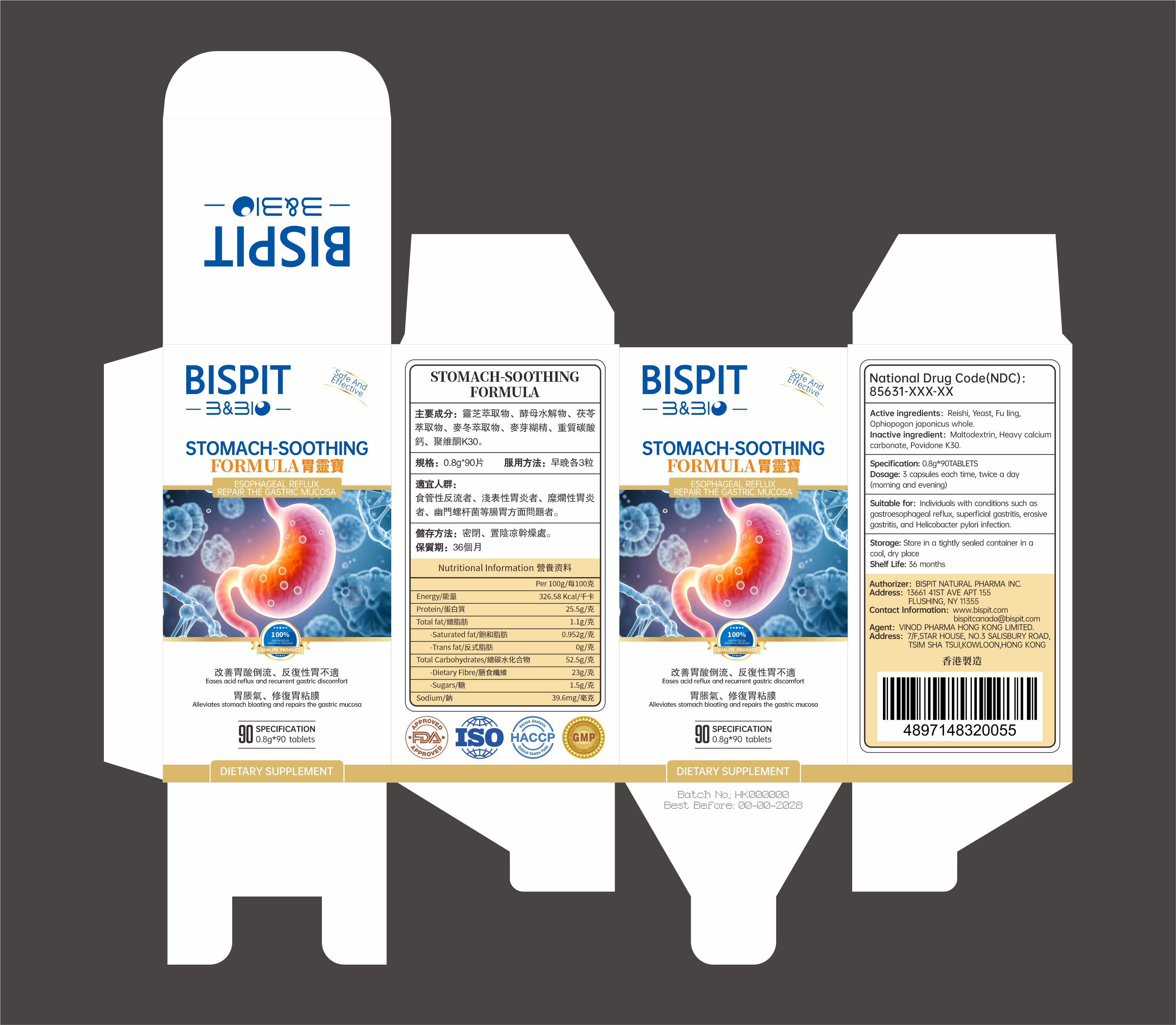 DRUG LABEL: STOMACH-SOOTHING FORMULA
NDC: 85631-015 | Form: CAPSULE
Manufacturer: Bispit Canada Ltd.
Category: otc | Type: HUMAN OTC DRUG LABEL
Date: 20251221

ACTIVE INGREDIENTS: YEAST 3 g/100 g; OPHIOPOGON JAPONICUS WHOLE 4.5 g/100 g; REISHI 50 g/100 g; FU LING 5 g/100 g
INACTIVE INGREDIENTS: MALTODEXTRIN; POVIDONE K30; CALCIUM CARBONATE

85631-015-01STOMACH-SOOTHING FORMULA

ACTIVE INGREDIENT

Active ingredients: Reishi, Yeast, Fu ling,Ophiopogon japonicus whole.

Keep OUT OF CHILDREN TO REACH

PURPOSE

Alleviates stomach bloating and repairs the gastric mucosa

WARNINGS

Suitable for: individuals with conditions such asgastroesophageal reflux, superficial gastritis, erosivegastritis, and Helicobacter pylori infection.

inactive ingredient: Matodextrin, Heavy calciumarbonate,Povidone K30

DOSAGE AND ADMINISTRATION

0.8g 90 TABL FTS

INDICATIONS AND USAGE

Dosage: 3 capsules each time, twice a day(morning and evening)